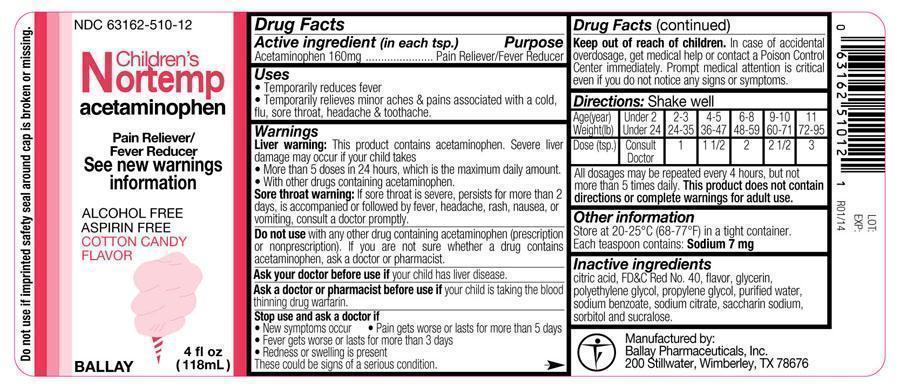 DRUG LABEL: Childrens Nortemp
NDC: 63162-510 | Form: SOLUTION
Manufacturer: Ballay Pharmaceuticals, Inc
Category: otc | Type: HUMAN OTC DRUG LABEL
Date: 20140624

ACTIVE INGREDIENTS: ACETAMINOPHEN 160 mg/5 mL
INACTIVE INGREDIENTS: ANHYDROUS CITRIC ACID; FD&C RED NO. 40; GLYCERIN; POLYETHYLENE GLYCOL 400; PROPYLENE GLYCOL; SODIUM BENZOATE; SODIUM CITRATE; SACCHARIN SODIUM DIHYDRATE; SORBITOL; SUCRALOSE; WATER

Childrens Nortemp

Drug Facts

Active Ingredient: Acetaminophen 160mg (in each 5 mL (tsp.))

Purpose

Purpose: Pain reliever/Fever reducer

Uses

■ Temporarily reduces fever

■ Temporarily relieves minor aches and pains associated with a cold, flu, sore throat, headache and toothache.

Warnings

Liver warning:This product contains acetaminophen. Severe liver damage may occur if your child takes:

■ more than 5 doses in 24 hours, which is the maximum daily amount

■ with other drugs containing acetaminophen

Sore throat warning: if sore throat is severe, persists for more than 2 days, is accompanied or followed by fever, headache, rash, nausea, or vomiting, consult a doctor promptly.

Do not use with any other drug containing acetaminophen (prescription or nonprescription). If you are not sure whether a drug contains acetaminophen, ask a doctor or pharmacist.

Ask a doctor before use if your child has liver disease.

Ask a doctor or pharmacist before use if your child is taking the blood thinning drug warfarin.

Stop use and ask a doctor if

■ new symptoms occur
■ redness or swelling is present
■ pain gets worse or lasts for more than 5 days
■ fever gets worse or lasts for more than 3 days.

These could be signs of serious condition.

Keep out of reach of children. In case of accidental overdose, get medical help or contact a Poison Control Center immediately . Prompt medical attention is critical even if you do not notice any signs or symptoms.

DOSAGE AND ADMINISTRATION

Directions: Shake well

Age (year); Weight (lb) | Under 2; Under 24 | 2 - 3; 24 - 35 | 4 - 5; 36 - 47 | 6 - 8; 48 - 59 | 9 - 10; 60 - 71 | 11; 72 - 95
Dose (tsp.) | Consult Doctor | 1 | 1 1/2 | 2 | 2 1/2 | 3

All dosages may be repeated every 4 hours, but not more than 5 times daily. this product does not contain directions or complete warnings for adult use.

Other information
Store between 20°-25°C (68°-77°F) in a tight container.

Each teaspoon contains: Sodium 7 mg

Inactive ingredients

citric acid, FD&C Red No. 40, flavor, glycerin, polyethylene glycol, propylene glycol, purified water, saccharin sodium, sodium benzoate, sodium citrate, sorbitol and sucralose.

Manufactured by:

Ballay Pharmaceuticals, Inc.

200 Stillwater

Wimberley, TX 78676